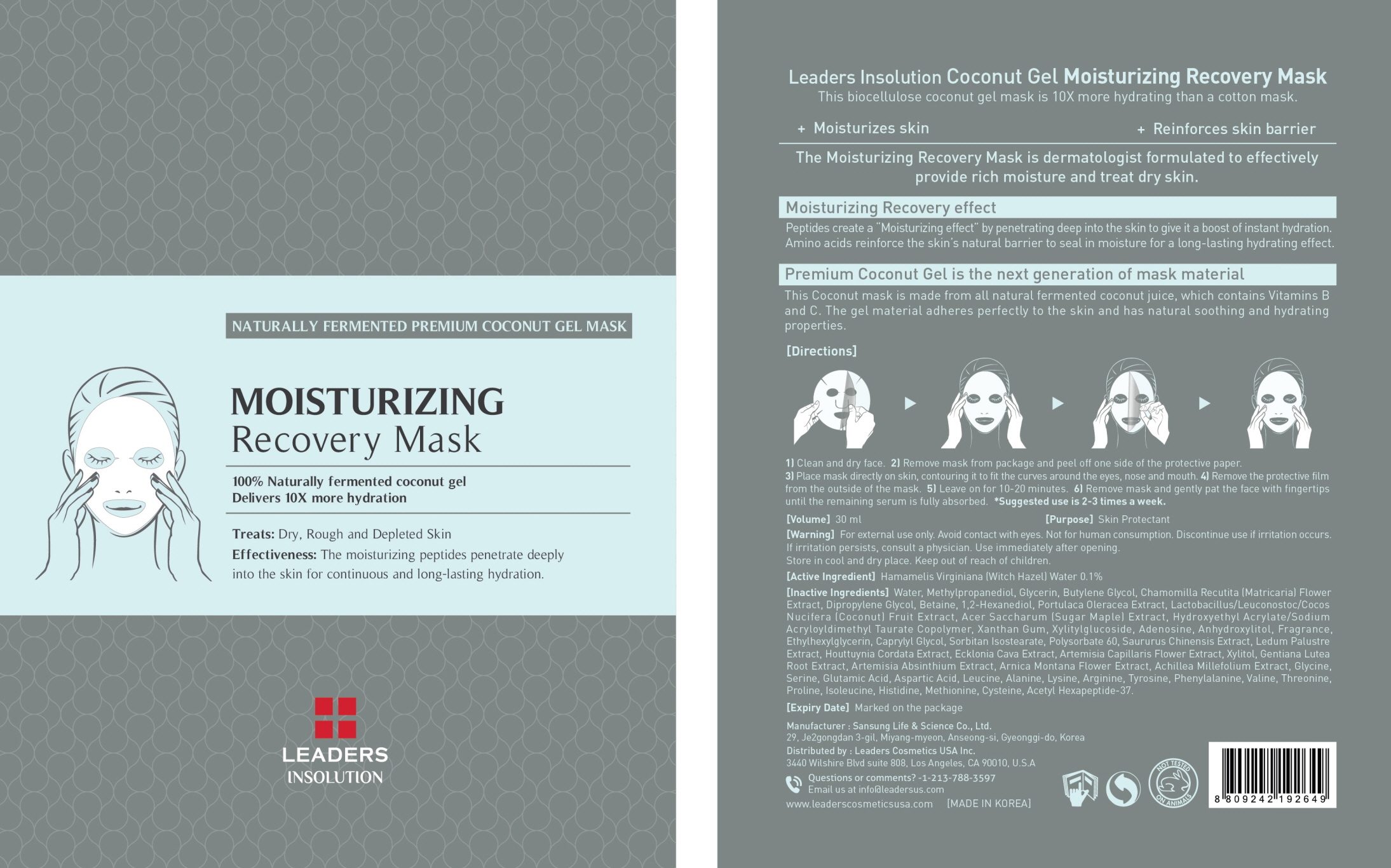 DRUG LABEL: Leaders Coconut Moisturizing Recovery Mask
NDC: 69424-400 | Form: PATCH
Manufacturer: SANSUNG LIFE & SCIENCE CO., LTD.
Category: otc | Type: HUMAN OTC DRUG LABEL
Date: 20160129

ACTIVE INGREDIENTS: Witch Hazel 30 mg/30 mL
INACTIVE INGREDIENTS: Water; Methylpropanediol

ACTIVE INGREDIENT

[Active Ingredient] Hamamelis Virginiana (Witch Hazel) Water 0.1%

INACTIVE INGREDIENT

[Inactive Ingredients] Water, Methylpropanediol, Glycerin, Butylene Glycol, Chamomilla Recutita (Matricaria) Flower Extract, Dipropylene Glycol, Betaine, 1,2-Hexanediol, Portulaca Oleracea Extract, Lactobacillus/Leuconostoc/Cocos Nucifera (Coconut) Fruit Extract, Acer Saccharum (Sugar Maple) Extract, Hydroxyethyl Acrylate/Sodium Acryloyldimethyl Taurate Copolymer, Xanthan Gum, Xylitylglucoside, Adenosine, Anhydroxylitol, Fragrance, Ethylhexylglycerin, Caprylyl Glycol, Sorbitan Isostearate, Polysorbate 60, Saururus Chinensis Extract, Ledum Palustre Extract, Houttuynia Cordata Extract, Ecklonia Cava Extract, Artemisia Capillaris Flower Extract, Xylitol, Gentiana Lutea Root Extract, Artemisia Absinthium Extract, Arnica Montana Flower Extract, Achillea Millefolium Extract, Glycine, Serine, Glutamic Acid, Aspartic Acid, Leucine, Alanine, Lysine, Arginine, Tyrosine, Phenylalanine, Valine, Threonine, Proline, lsoleucine, Histidine, Methionine, Cysteine, Acetyl Hexapeptide-37

PURPOSE

[Purpose] Skin Protectant

WARNINGS

[Warning] For external use only. Avoid contact with eyes. Not for human consumption. Discontinue use if irritation occurs. If irritation persists, consult a physician. Use immediately after opening. Store in cool and dry place. Keep out of reach of children.

KEEP OUT OF REACH OF CHILDREN

Directions

[Directions] 1) Clean and dry face. 2) Remove mask from package and peel off one side of the protective paper. 3) Place mask directly on skin, contouring it to fit the curves around the eyes, nose and mouth. 4) Remove the protective film from the outside of the mask. 5) Leave on for 10-20 minutes. 6) Remove mask and gently pat the face with fingertips until the remaining serum is fully absorbed. *Suggested use is 2-3 times a week.

Directions

[Directions] 1) Clean and dry face. 2) Remove mask from package and peel off one side of the protective paper. 3) Place mask directly on skin, contouring it to fit the curves around the eyes, nose and mouth. 4) Remove the protective film from the outside of the mask. 5) Leave on for 10-20 minutes. 6) Remove mask and gently pat the face with fingertips until the remaining serum is fully absorbed. *Suggested use is 2-3 times a week.